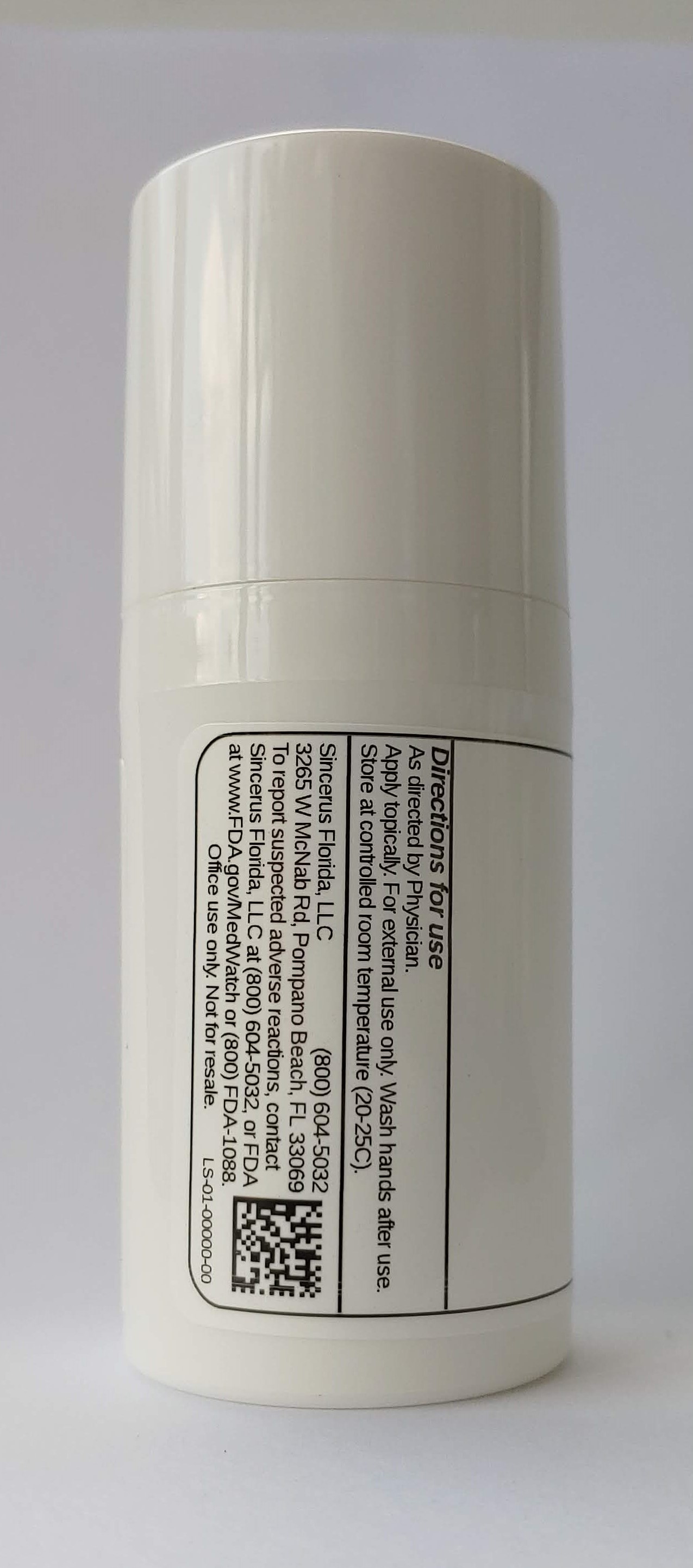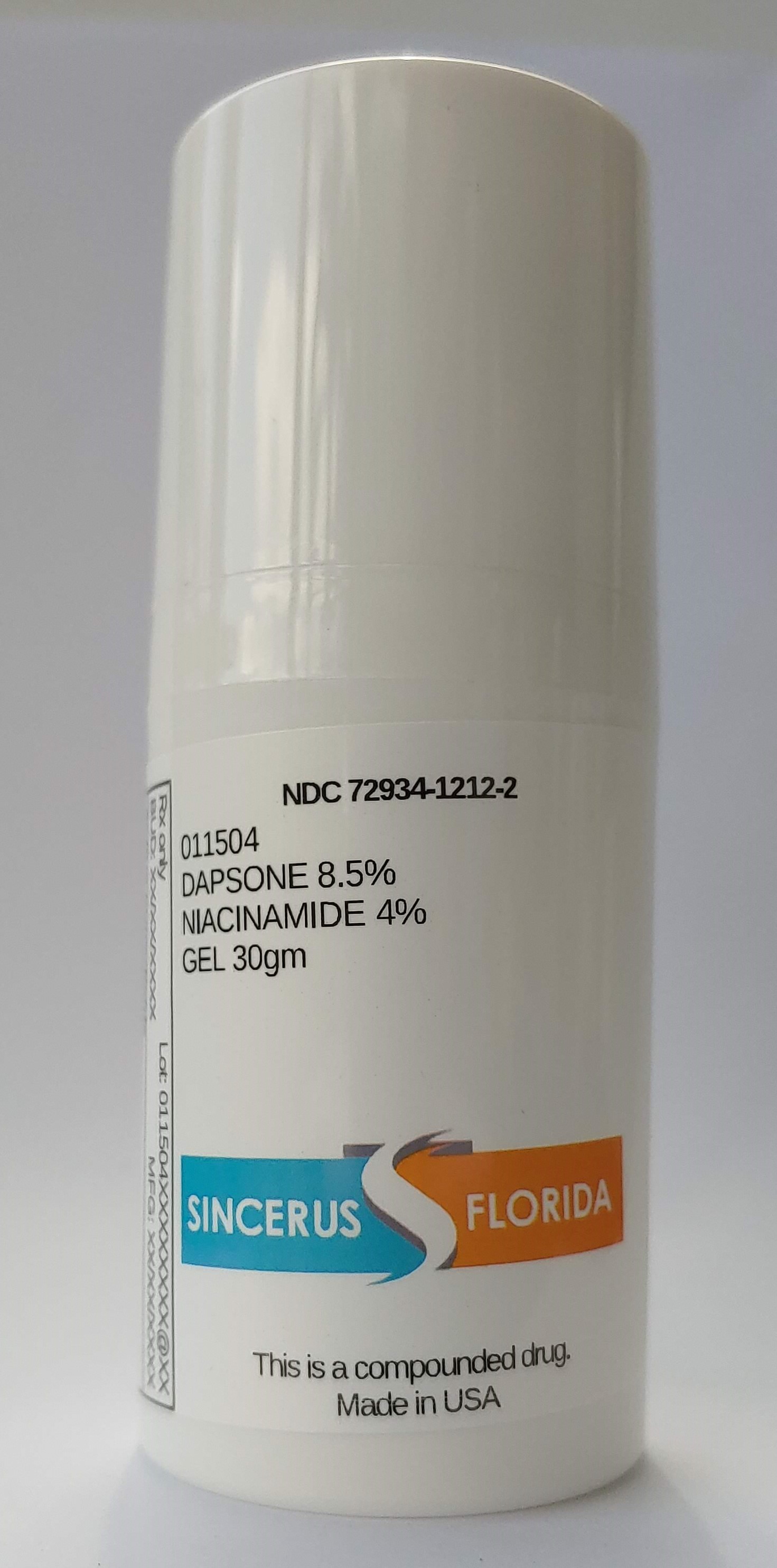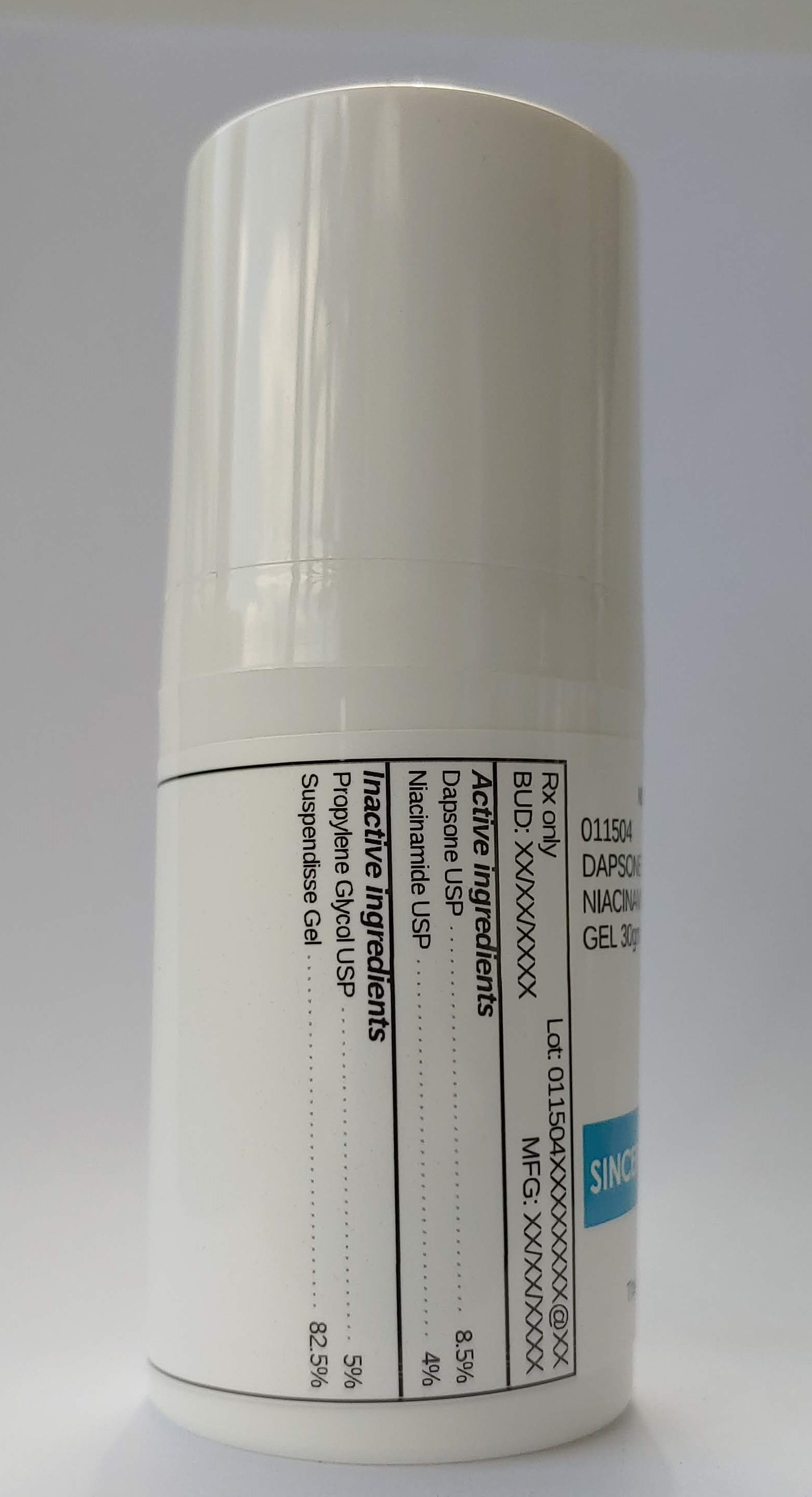 DRUG LABEL: 011504 DAPSONE 8.5% / NIACINAMIDE 4%
NDC: 72934-1212 | Form: GEL
Manufacturer: Sincerus Florida, LLC
Category: prescription | Type: HUMAN PRESCRIPTION DRUG LABEL
Date: 20200702

ACTIVE INGREDIENTS: DAPSONE 8.5 g/100 g; NIACINAMIDE 4 g/100 g

011504 DAPSONE 8.5% / NIACINAMIDE 4%